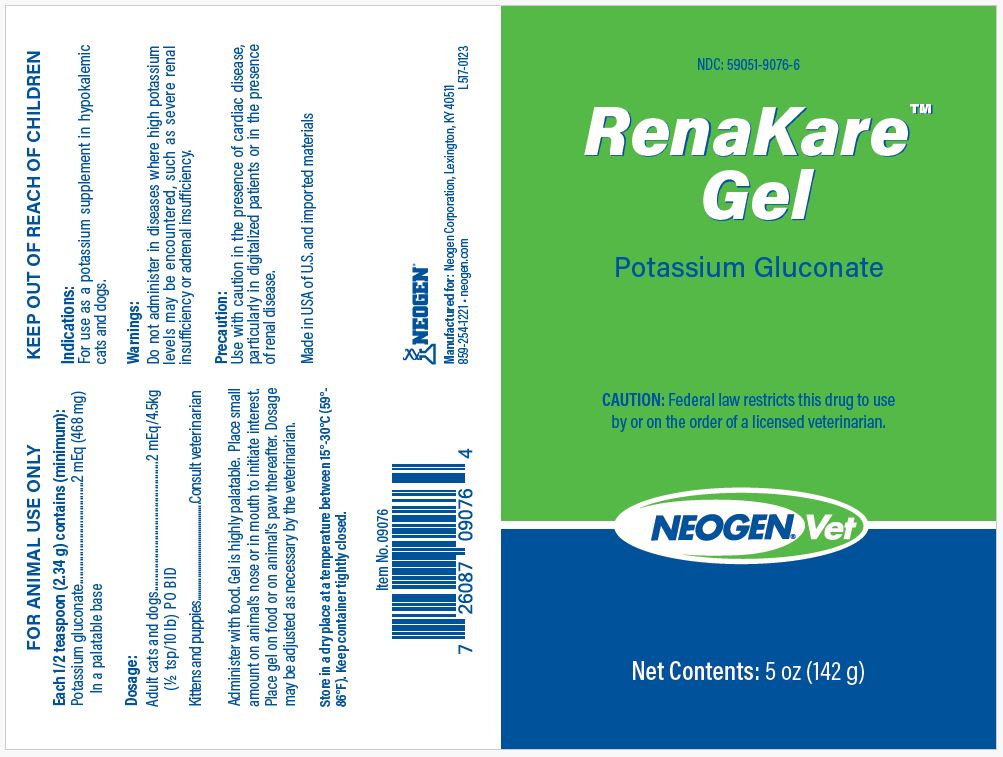 DRUG LABEL: RenaKare
NDC: 59051-9076 | Form: GEL
Manufacturer: Neogen Corporation-Mercer Rd
Category: animal | Type: PRESCRIPTION ANIMAL DRUG LABEL
Date: 20240123

ACTIVE INGREDIENTS: POTASSIUM GLUCONATE 468 mg/234 g

RenaKare Gel

DESCRIPTION

RenaKare™

Gel

Potassium Gluconate

CAUTION: Federal law restricts this drug to use by or on the order of a licensed veterinarian.

WARNINGS

FOR ANIMAL USE ONLY

DESCRIPTION

Each 1/2 teaspoon (2.34 g) contains (minimum):
Potassium gluconate............2 mEq (468 mg)
In a palatable base

Dosage:
Adult cats and dogs.....2 mEq/4.5 kg
(½ tsp/10 lb) PO BID

Kittens and puppies............Consult veterinarian

Administer with food. Gel is highly palatable. Place small amount on animal’s nose or in mouth to initiate interest. Place gel on food or on animal’s paw thereafter. Dosage may be adjusted as necessary by the veterinarian.

STORAGE AND HANDLING

Store in a dry place at a temperature between 15°-30°C (59°-86°F). Keep container tightly closed.

UPC
7 26087 09076 4

Indications:

For use as a potassium supplement in hypokalemic cats and dogs.

Warnings:

Do no administer in diseases where high potassium levels may be encountered, such as severe renal insufficiency or adrenal insufficiency.

Precaution:

Use with caution in the presence of cardiac disease, particularly in digitalized patients or in the presence of renal disease.

Manufactured for Neogen Corporation

Lexington, KY 40511

859-254-1221 neogen.com

PRINCIPAL DISPLAY PANEL - 5 oz Bottle

NDC: 59051-9076-6

RenaKare™

Gel

Potassium Gluconate

CAUTION: Federal law restricts this drug to use by or on the order of a licensed veterinarian.

NEOGEN® Vet

Net Contents: 5 oz (142 g)